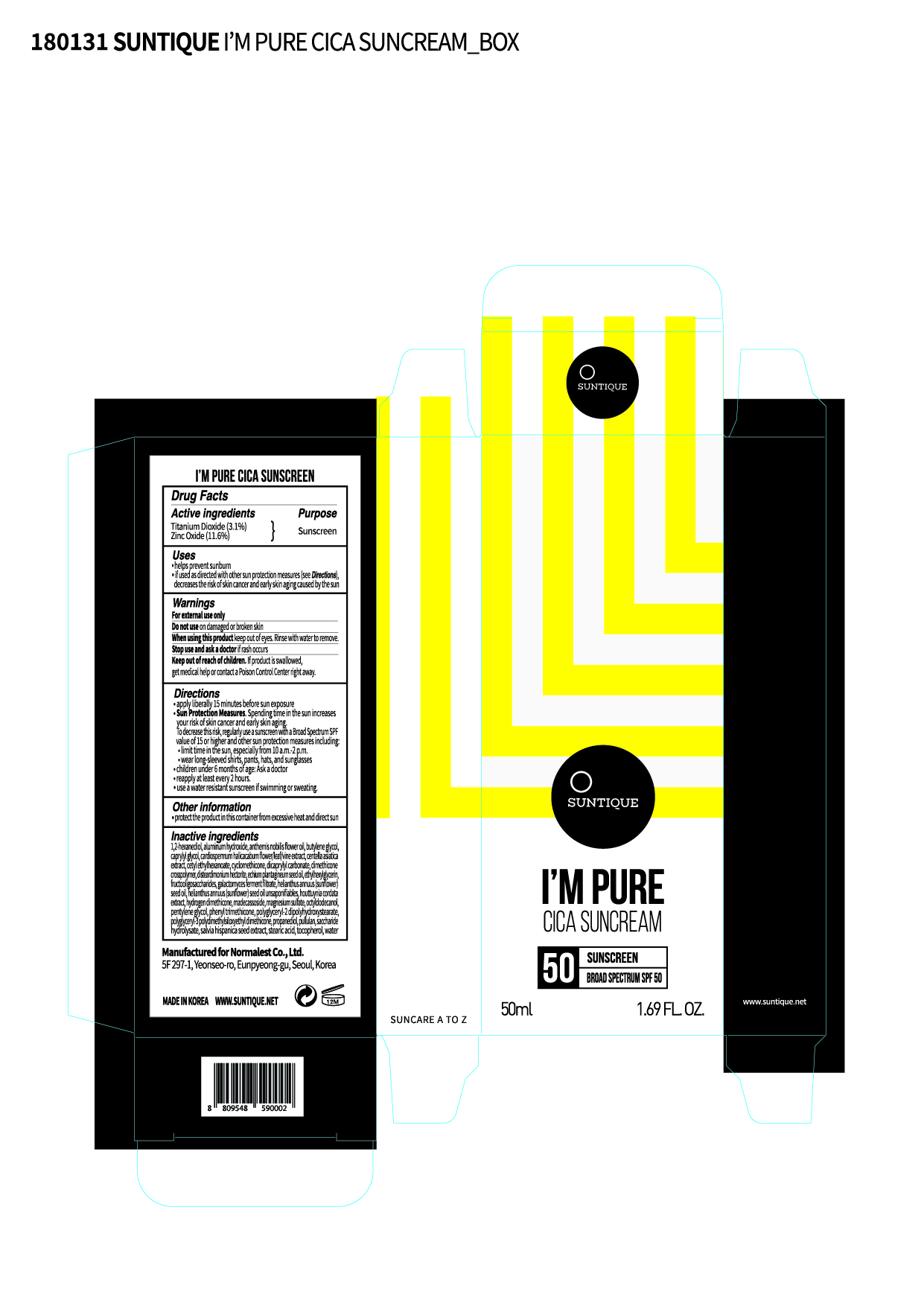 DRUG LABEL: IM PURE CICA SUNSCREEN
NDC: 72284-0004 | Form: LOTION
Manufacturer: Normalest Co., Ltd.
Category: otc | Type: HUMAN OTC DRUG LABEL
Date: 20190306

ACTIVE INGREDIENTS: ZINC OXIDE 5.82 g/50 mL; TITANIUM DIOXIDE 1.56 g/50 mL
INACTIVE INGREDIENTS: 1,2-HEXANEDIOL; SUNFLOWER SEED OIL GLYCERETH-8 ESTERS; CHAMOMILE FLOWER OIL; CARDIOSPERMUM HALICACABUM WHOLE; MADECASSOSIDE; HYDROGEN DIMETHICONE (13 CST); STEARIC ACID; PHENYL TRIMETHICONE; CENTELLA ASIATICA LEAF; INVERT SUGAR; CETYL ETHYLHEXANOATE; MAGNESIUM SULFATE ANHYDROUS; POLYGLYCERYL-2 DIPOLYHYDROXYSTEARATE; OCTYLDODECANOL; ECHIUM PLANTAGINEUM SEED OIL; WATER; CYCLOMETHICONE; ALUMINUM HYDROXIDE; DICAPRYLYL CARBONATE; PROPANEDIOL; POLYGLYCERYL-3 POLYDIMETHYLSILOXYETHYL DIMETHICONE (4000 MPA.S); DIMETHICONE CROSSPOLYMER (450000 MPA.S AT 12% IN CYCLOPENTASILOXANE); SALVIA HISPANICA SEED; HOUTTUYNIA CORDATA WHOLE; PULLULAN; DISTEARDIMONIUM HECTORITE; TOCOPHEROL; BUTYLENE GLYCOL; PENTYLENE GLYCOL; CAPRYLYL GLYCOL; FOSFRUCTOSE; ETHYLHEXYLGLYCERIN

PACKAGE LABEL

Active Ingredients
Zinc Oxide (11.6%)
Titanium Dioxide (3.1%)

Inactive Ingredients

Water, Cyclomethicone, Hydrogen Dimethicone, Aluminum Hydroxide, Stearic Acid, Dicaprylyl Carbonate, Propanediol, Polyglyceryl-3 Polydimethylsiloxyethyl Dimethicone, Dimethicone Crosspolymer, Phenyl Trimethicone, Salvia Hispanica Seed Extract, Centella Asiatica Extract, Houttuynia Cordata Extract, 1,2-Hexanediol, Saccharide Hydrolysate, Fructooligosaccharides, Pullulan, Cetyl Ethylhexanoate, Disteardimonium Hectorite, Magnesium Sulfate, Polyglyceryl-2 Dipolyhydroxystearate, Helianthus Annuus (Sunflower) Seed Oil, Anthemis Nobilis Flower Oil, Ethylhexylglycerin, Octyldodecanol, Echium Plantagineum Seed Oil, Cardiospermum Halicacabum Flower/Leaf/Vine Extract, Helianthus Annuus (Sunflower) Seed Oil Unsaponifiables, Tocopherol, Galactomyces Ferment Filtrate, Butylene Glycol, Pentylene Glycol, Caprylyl Glycol, Madecassoside